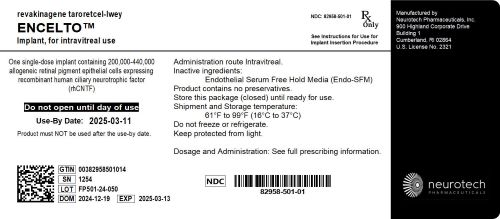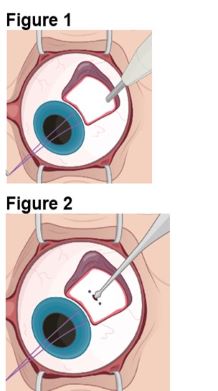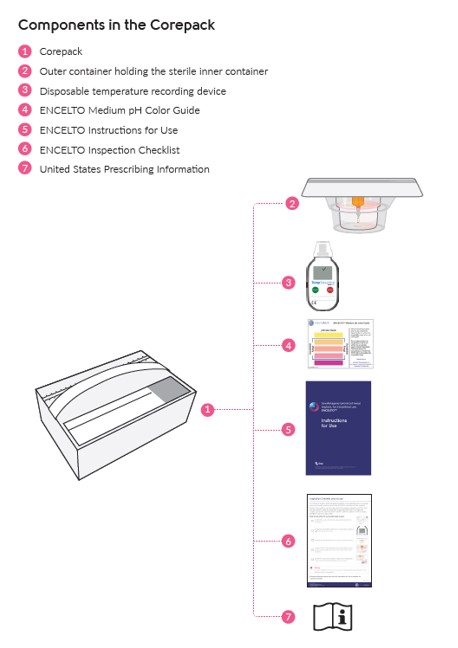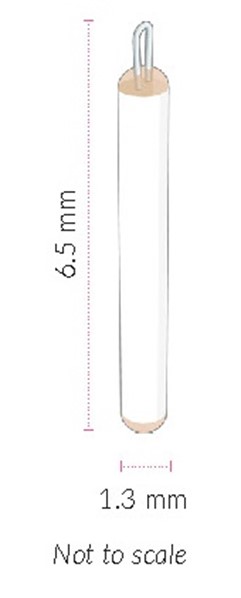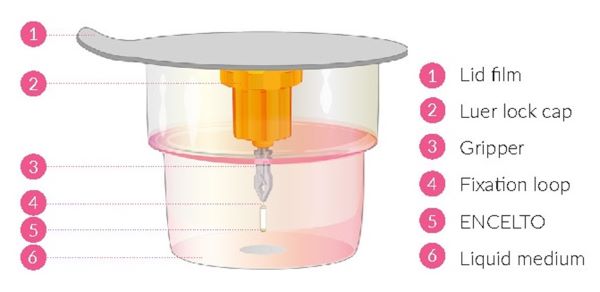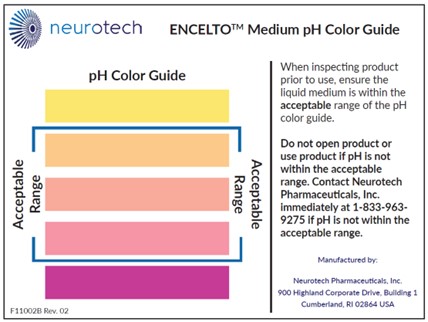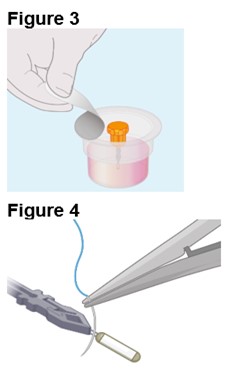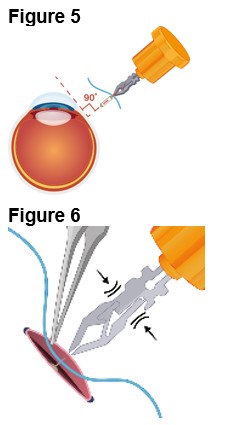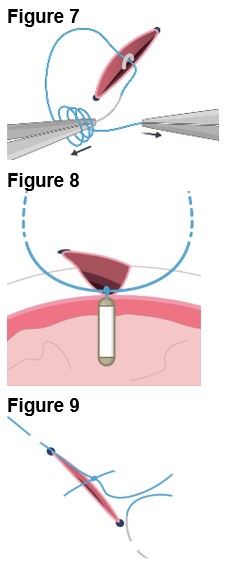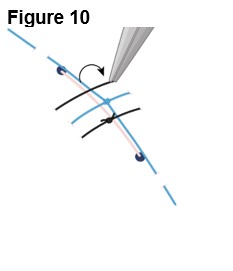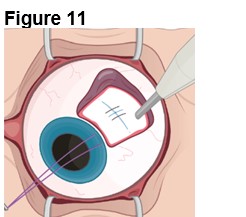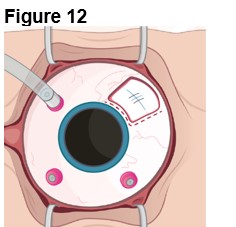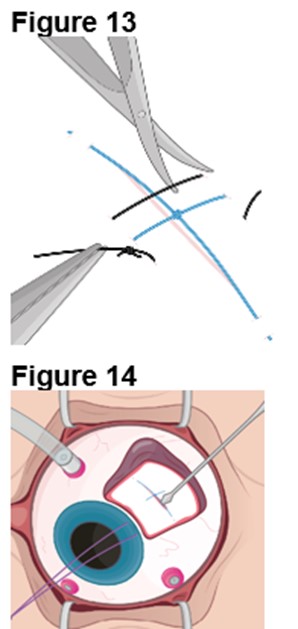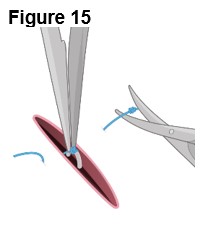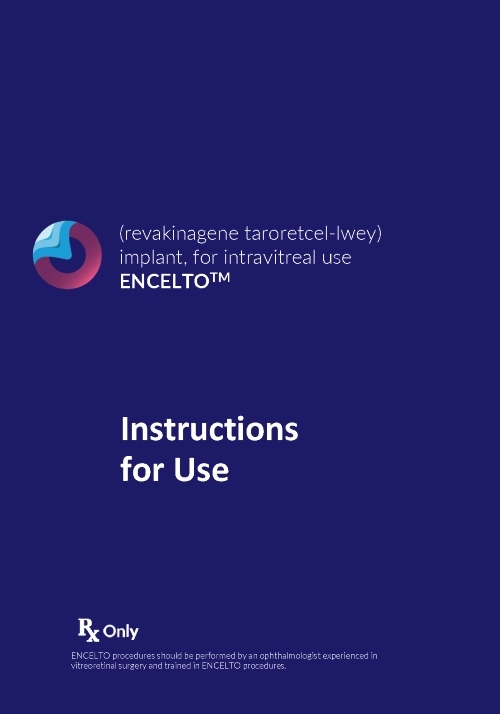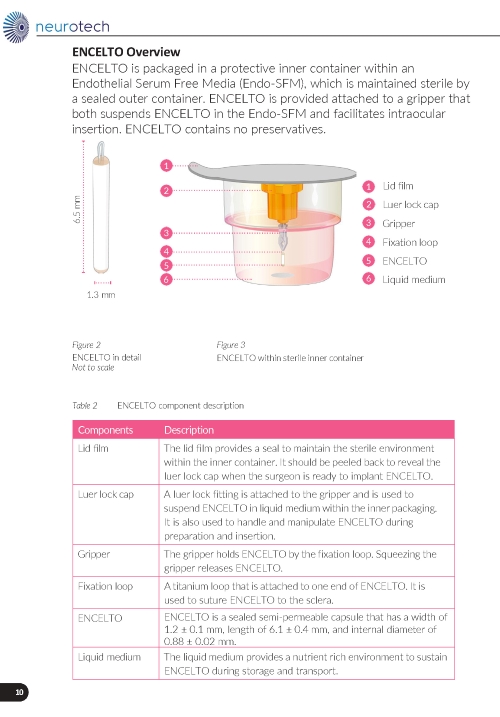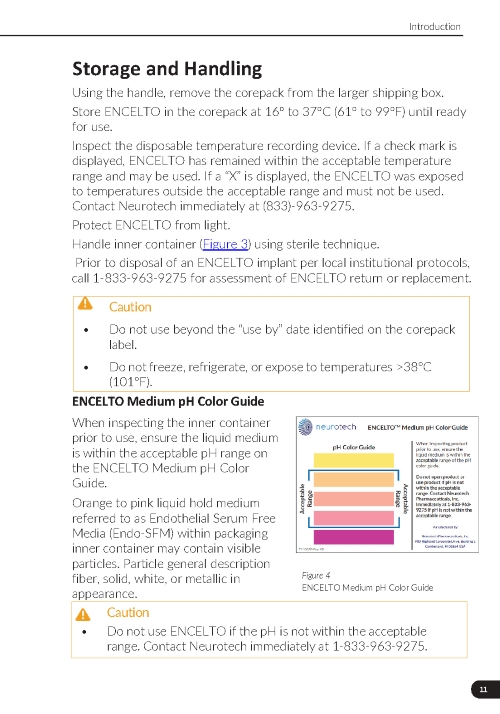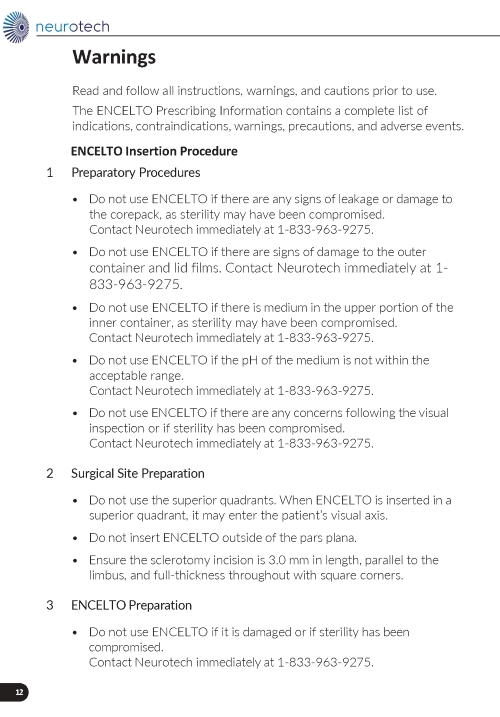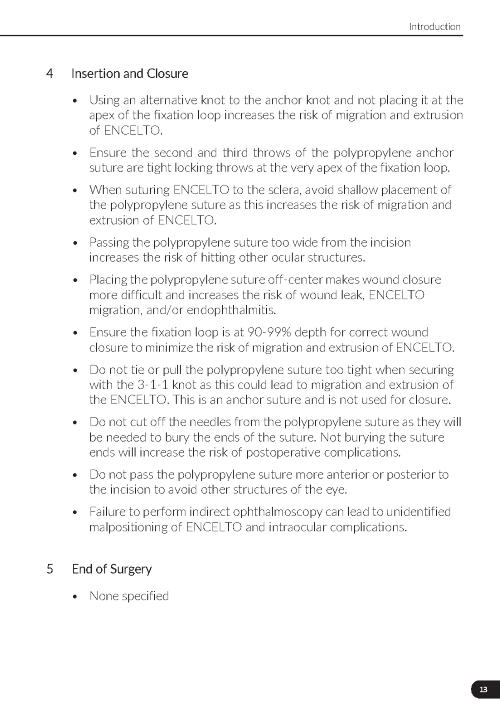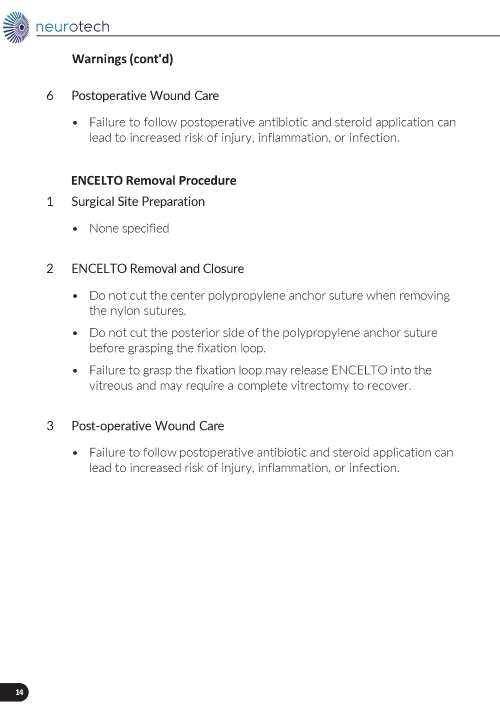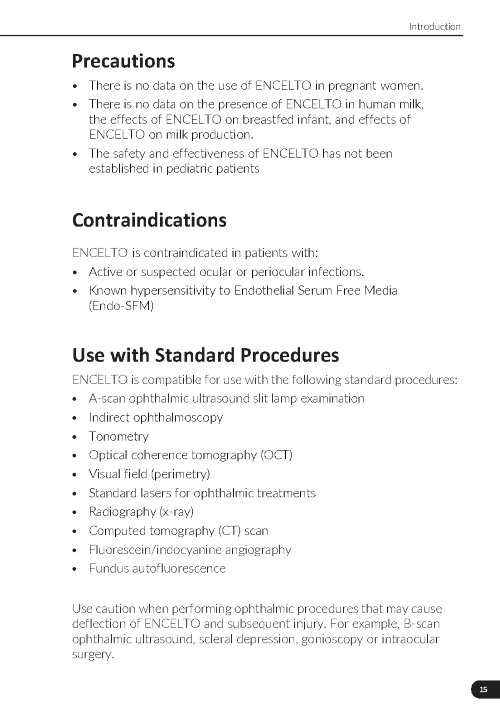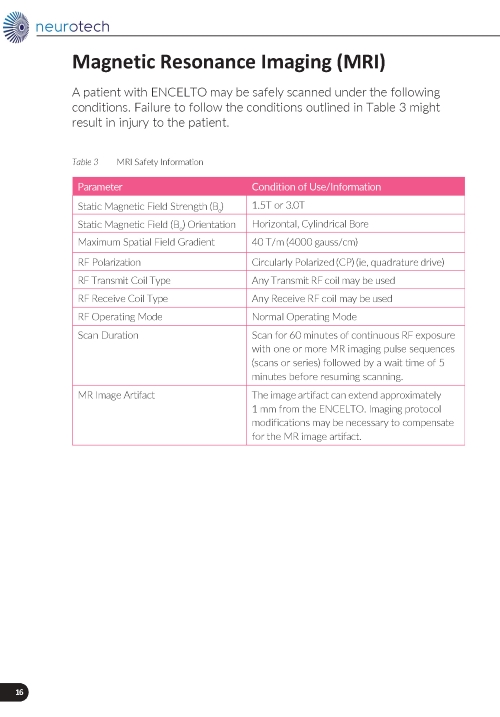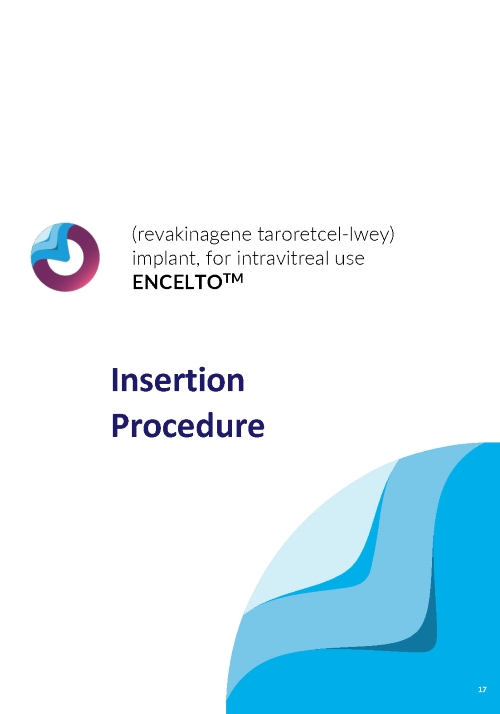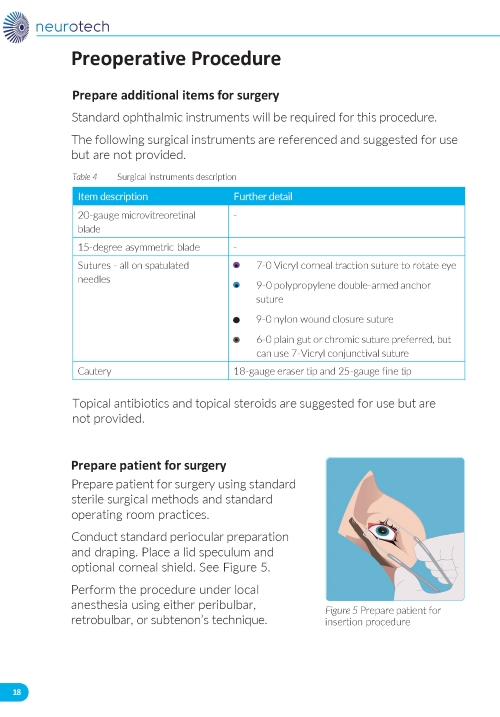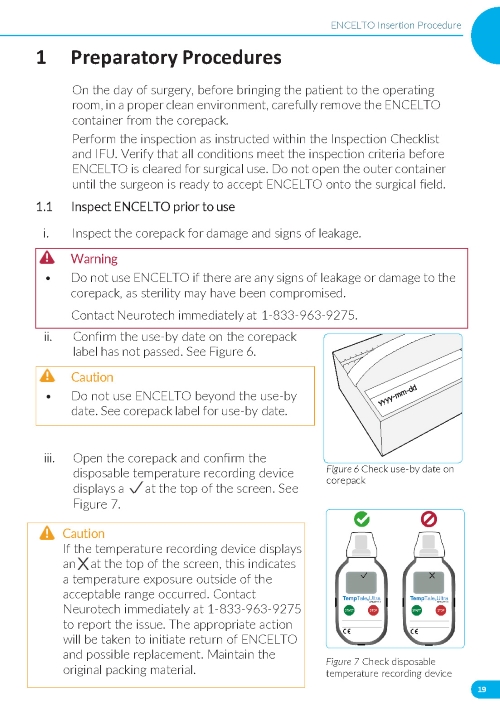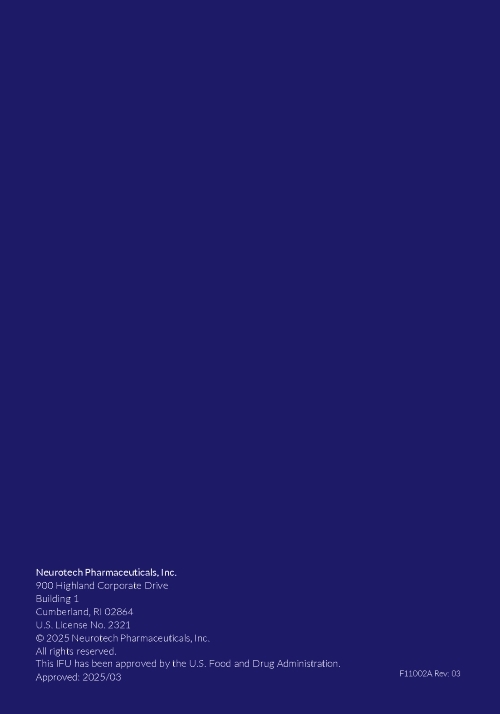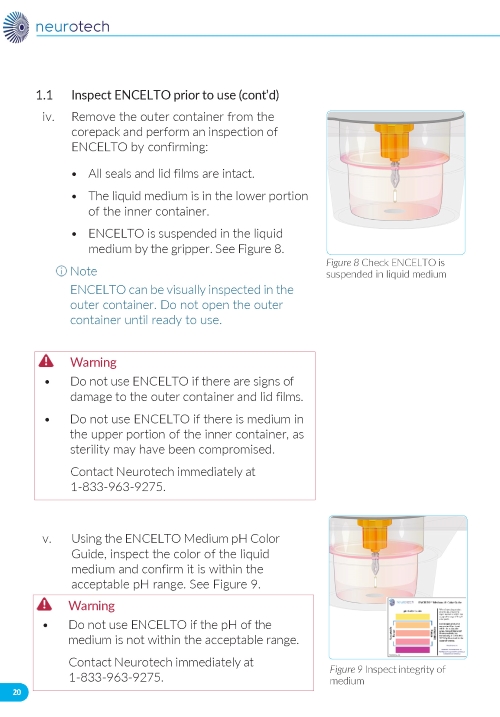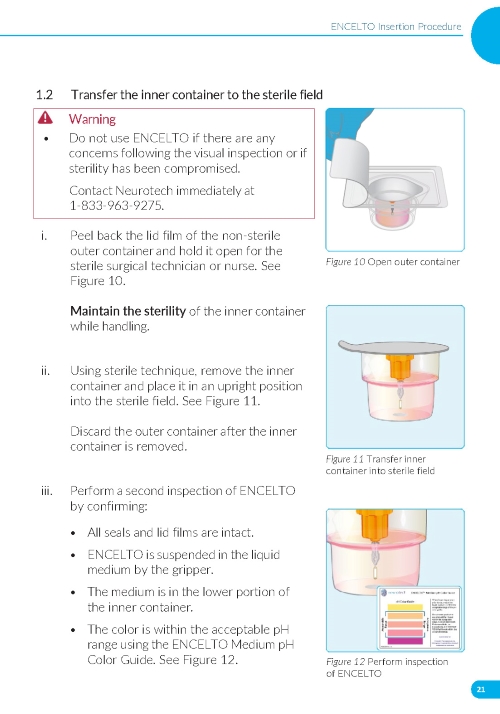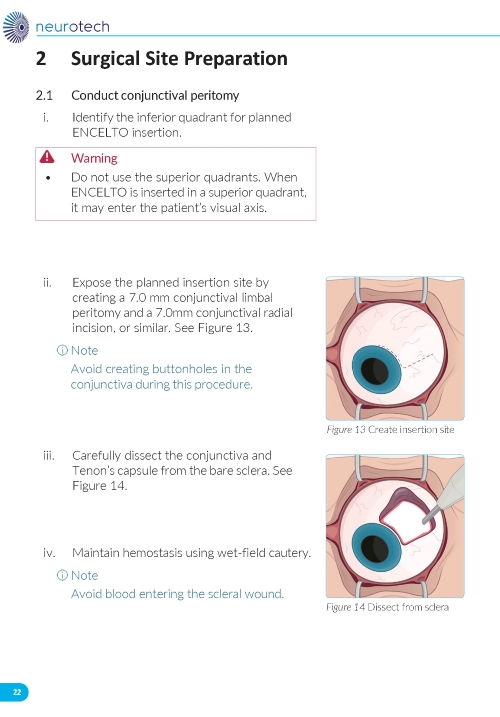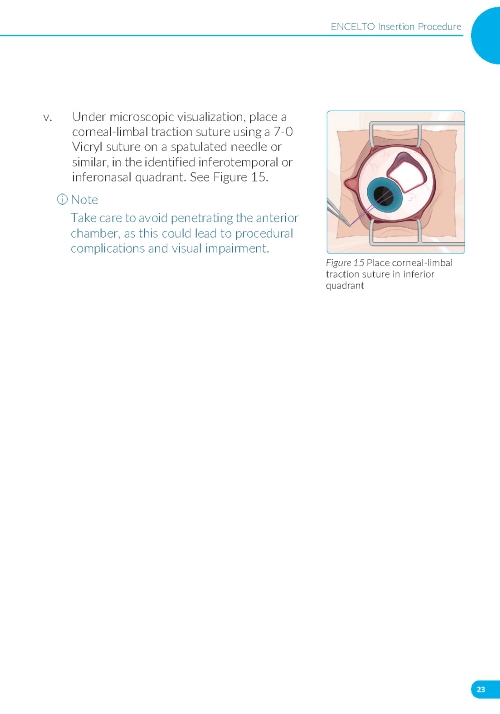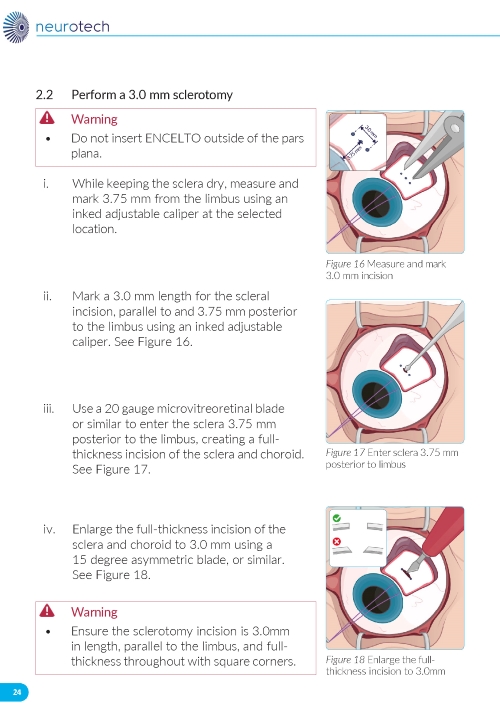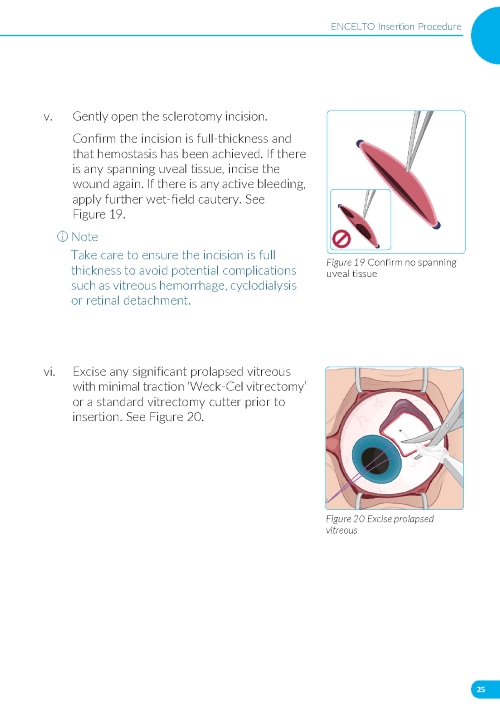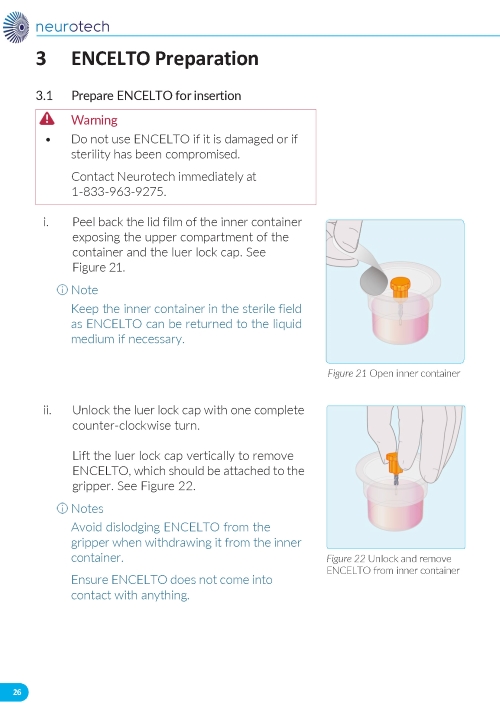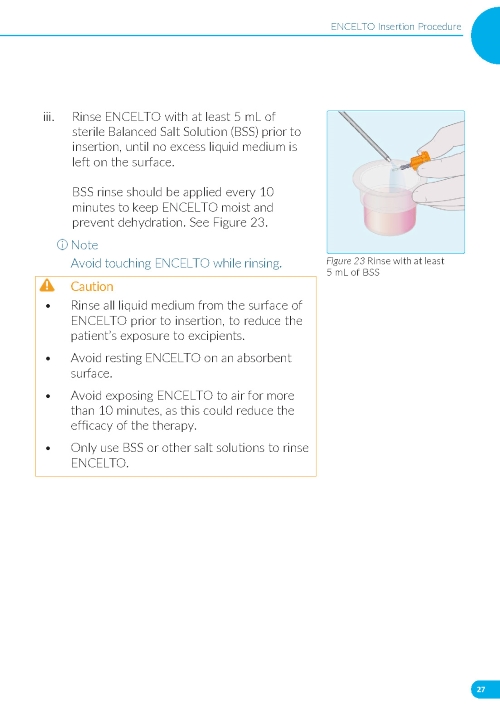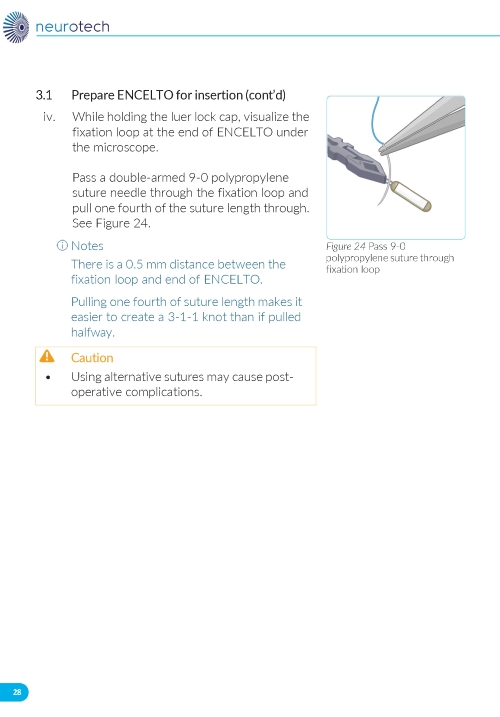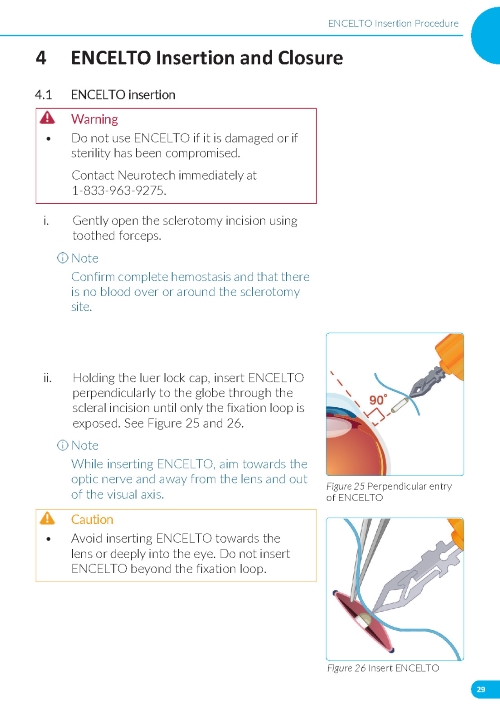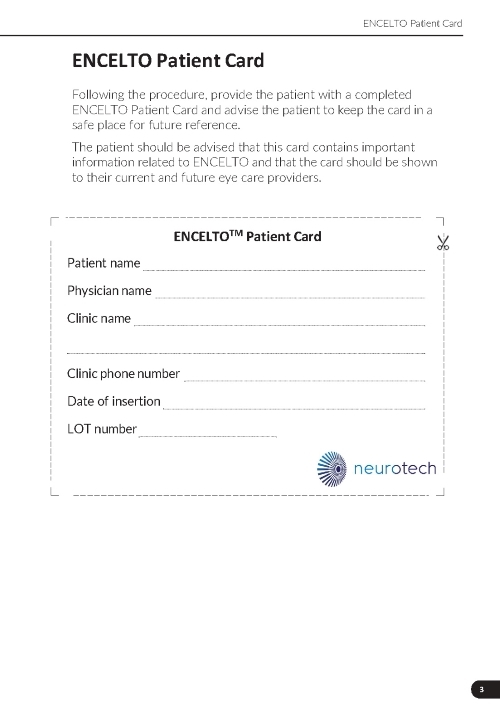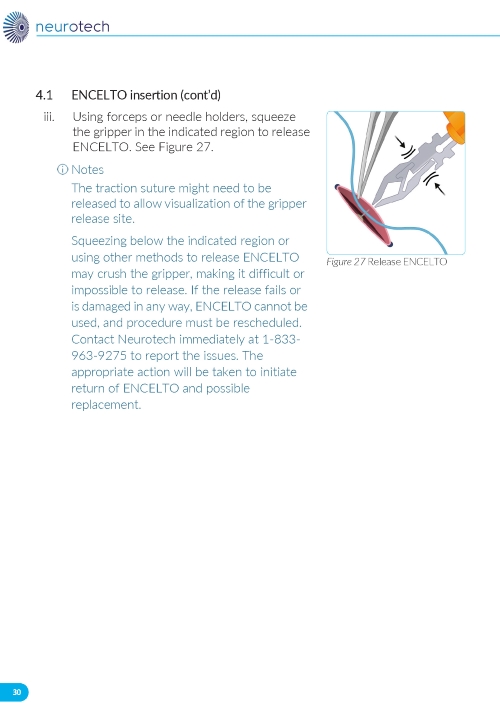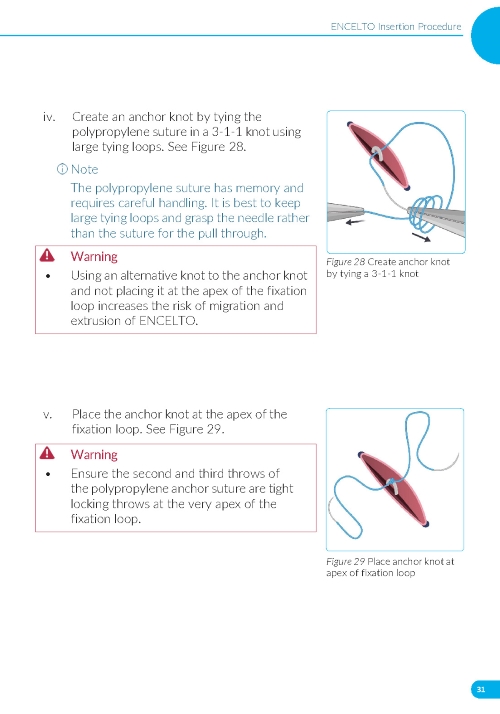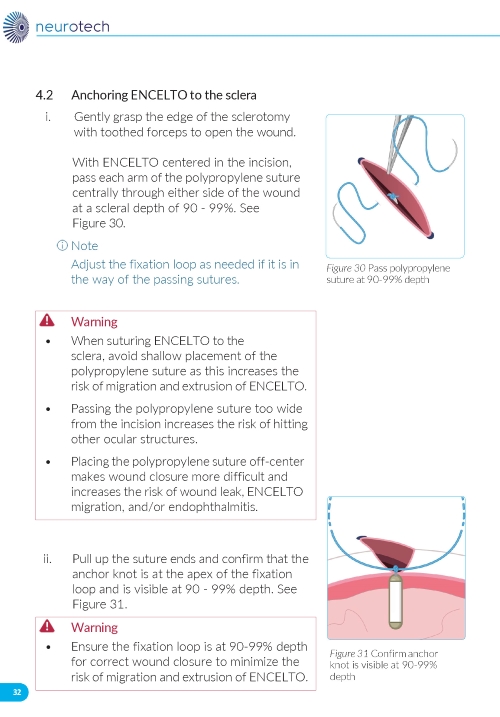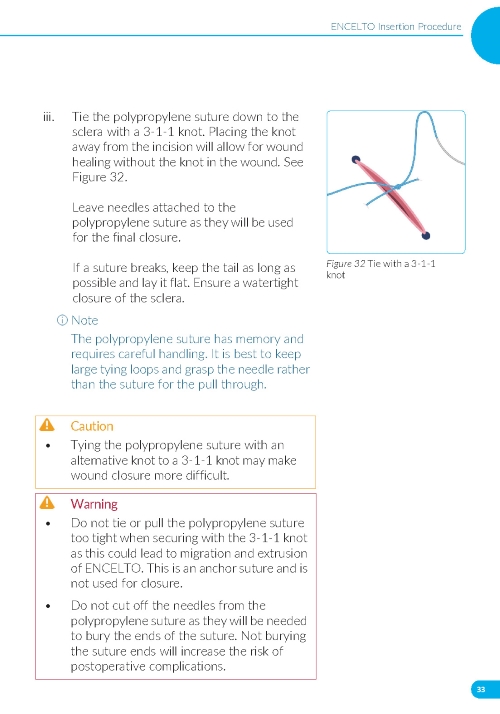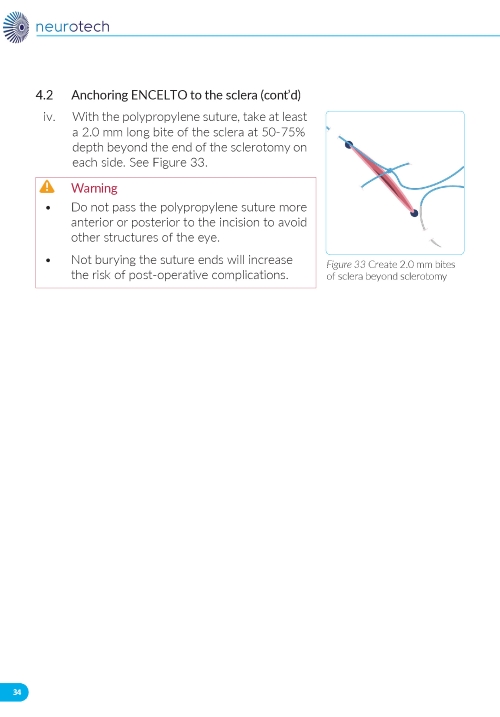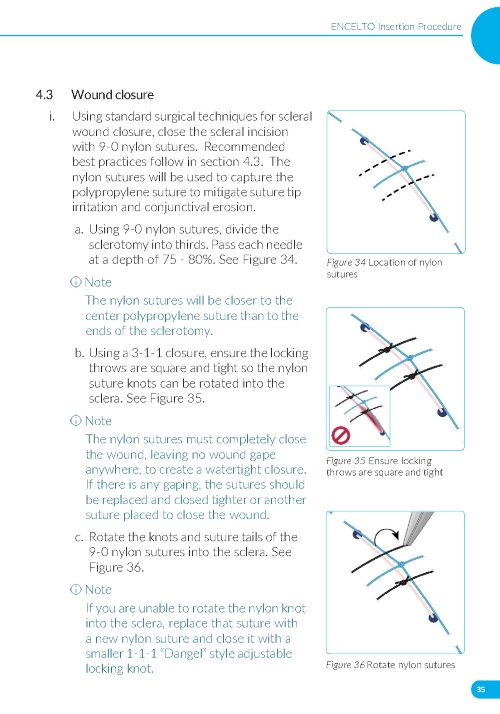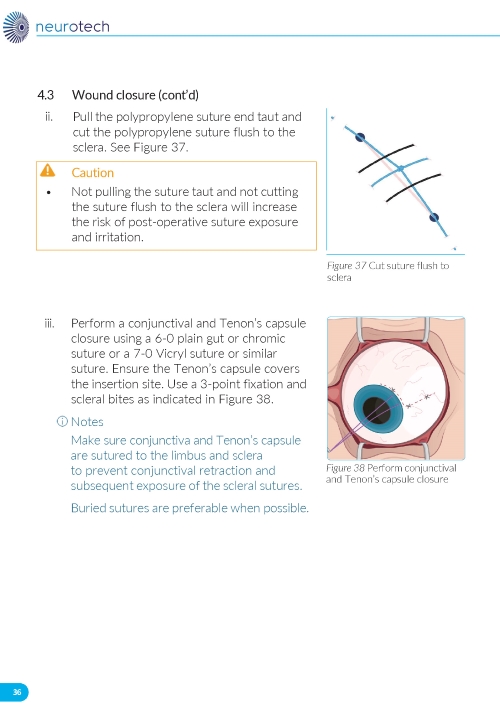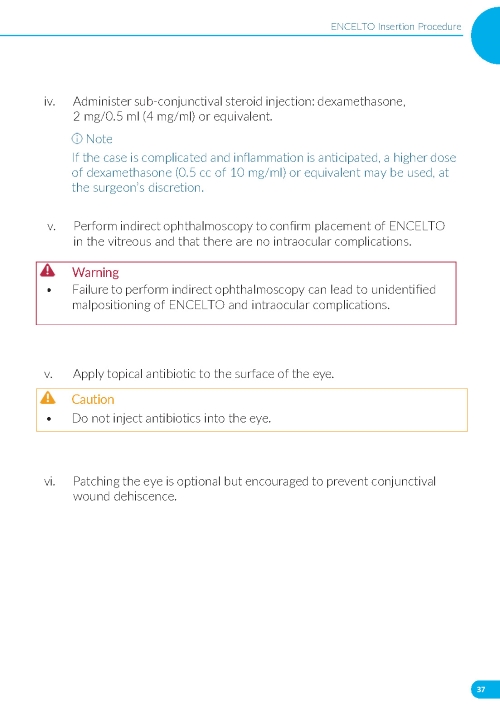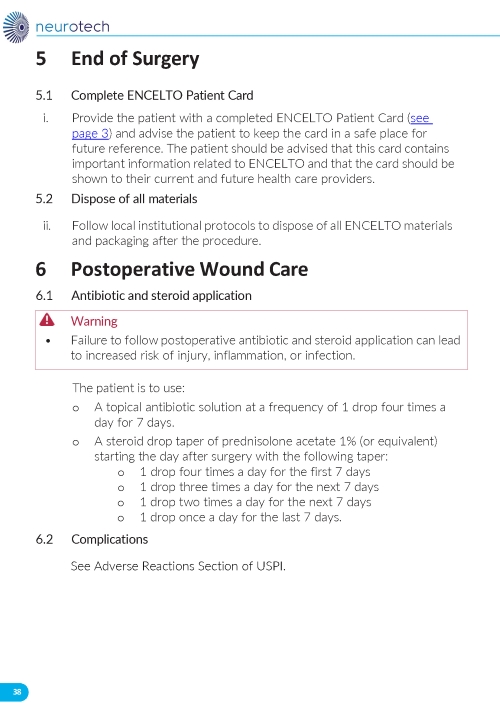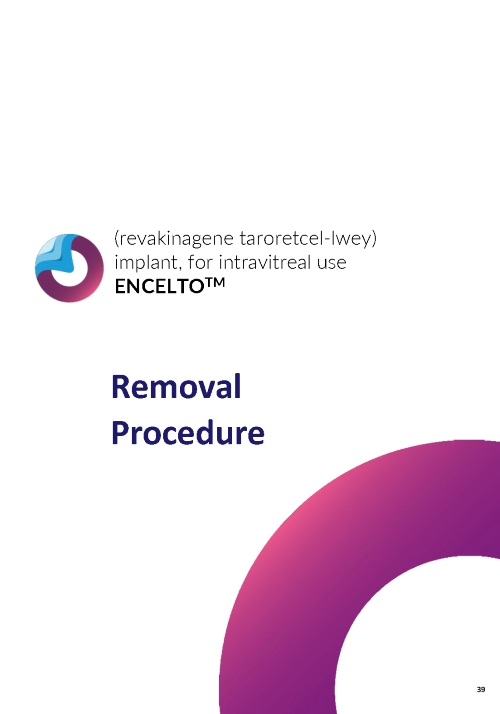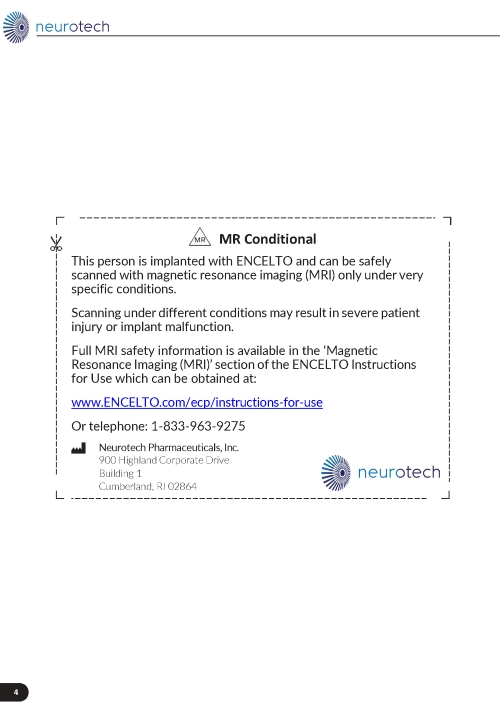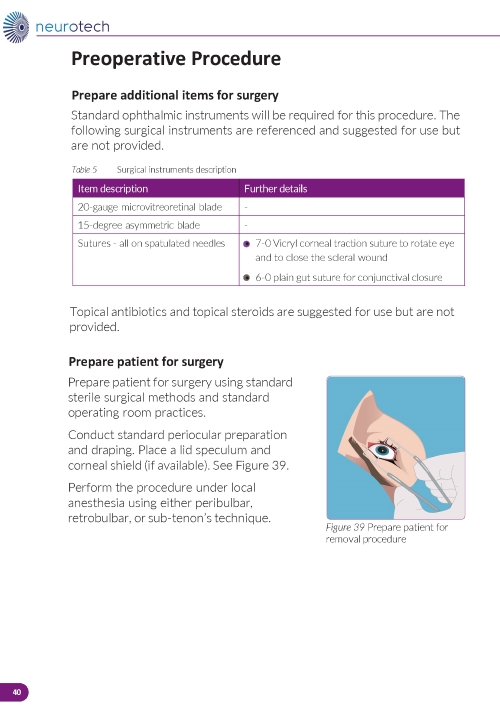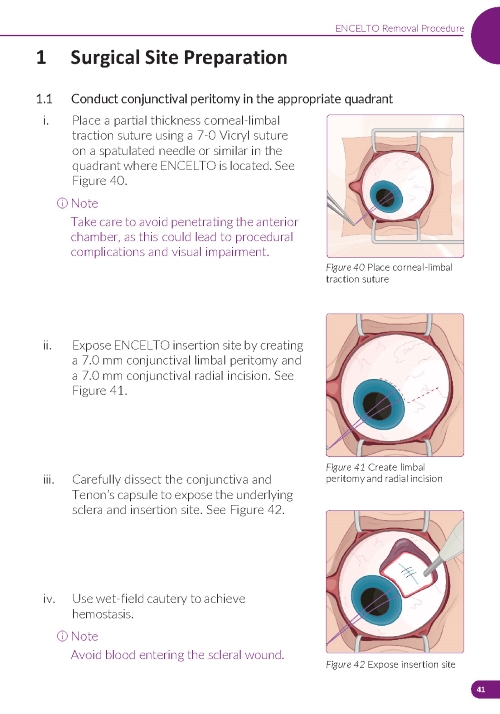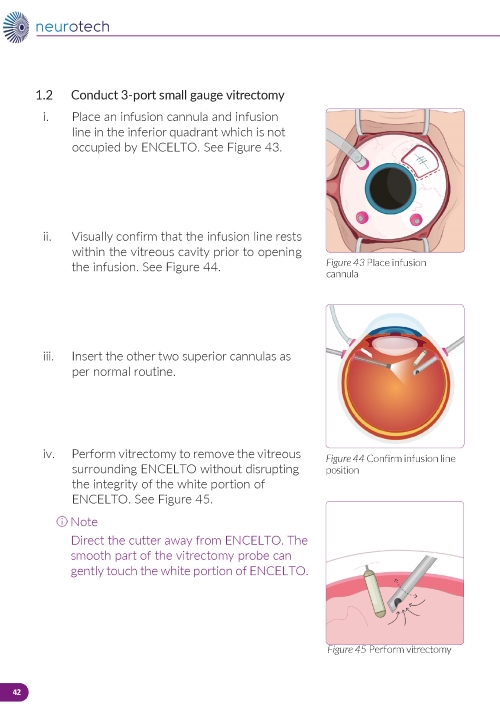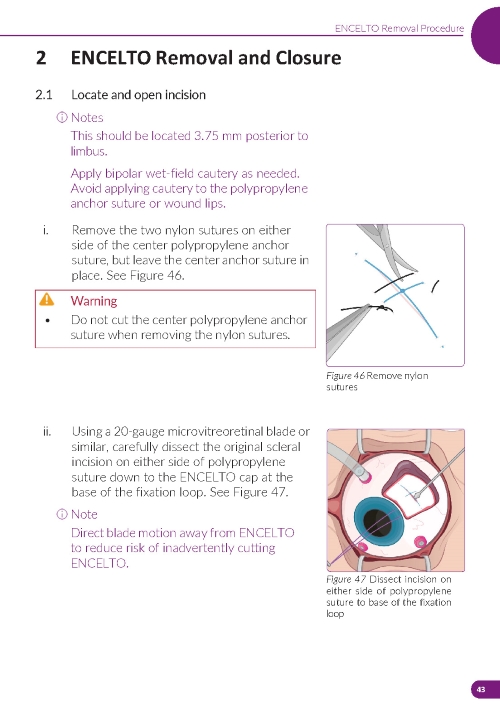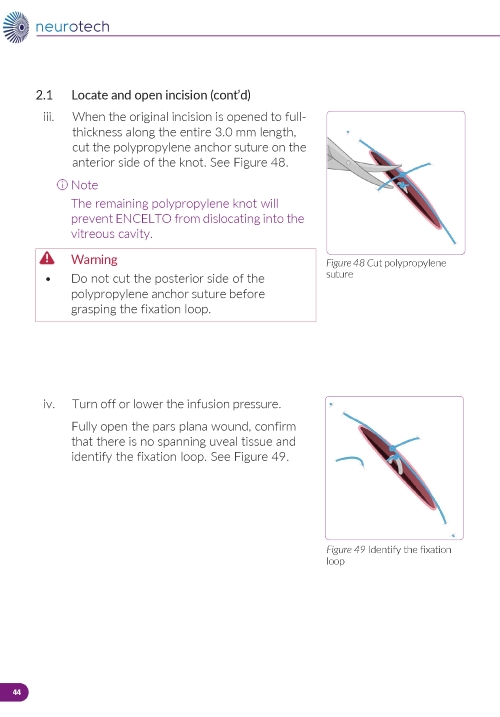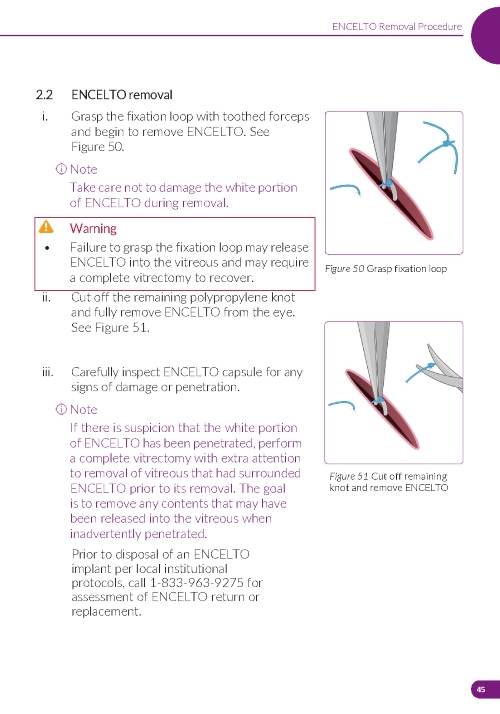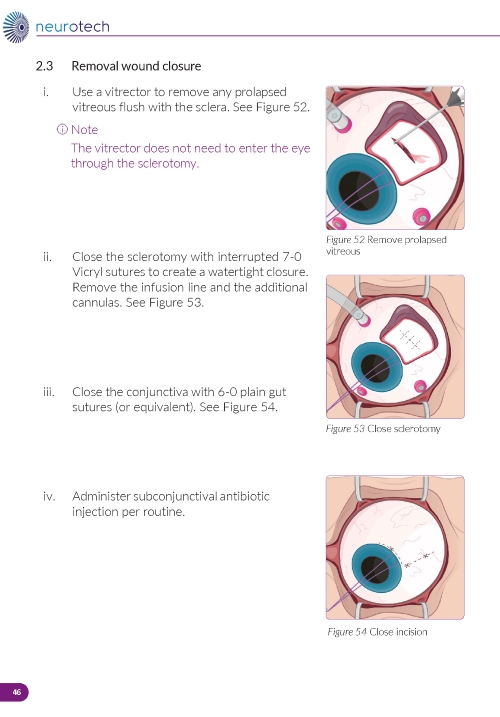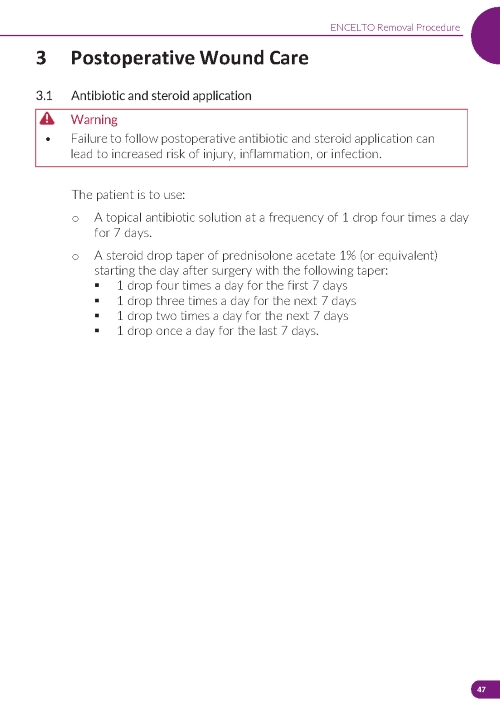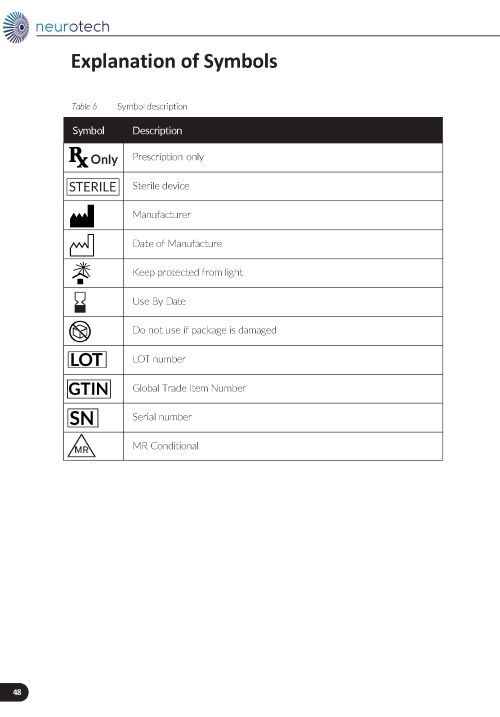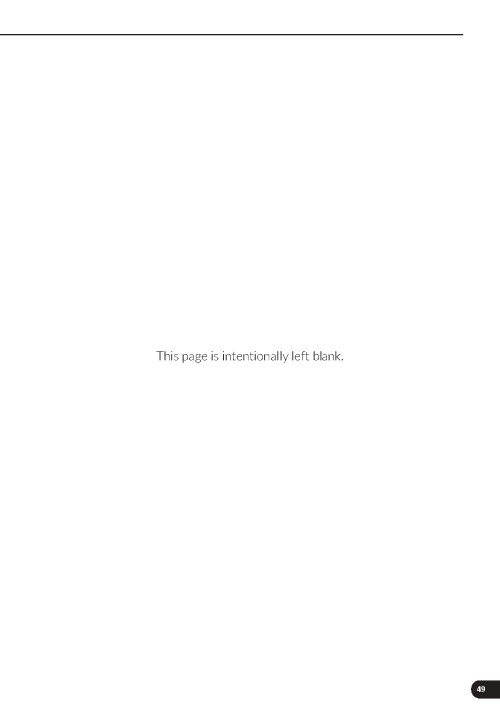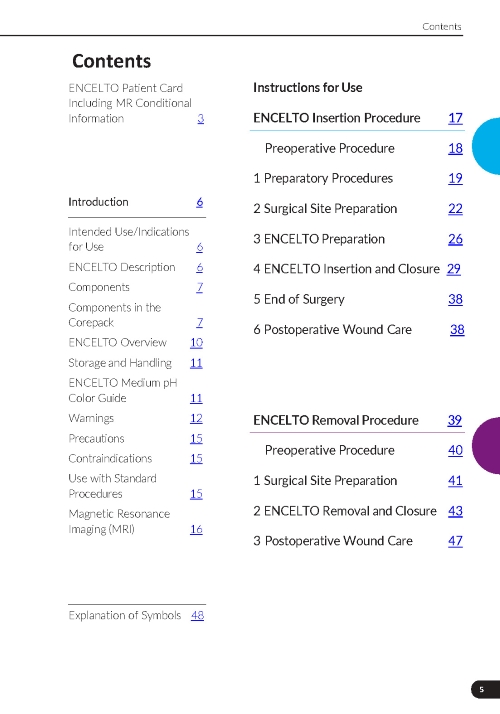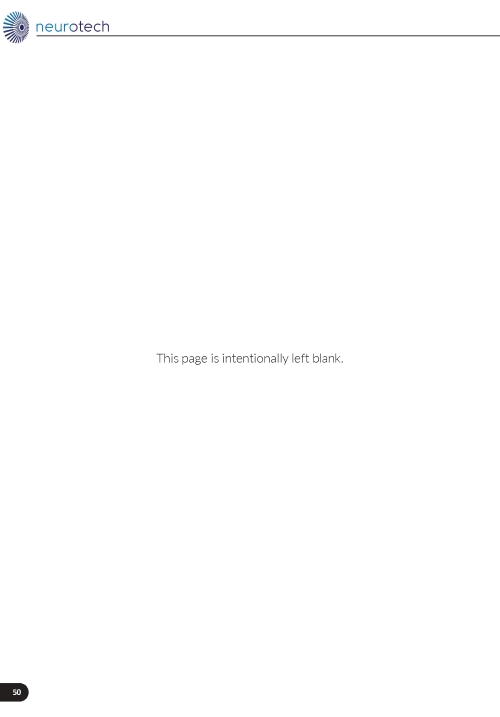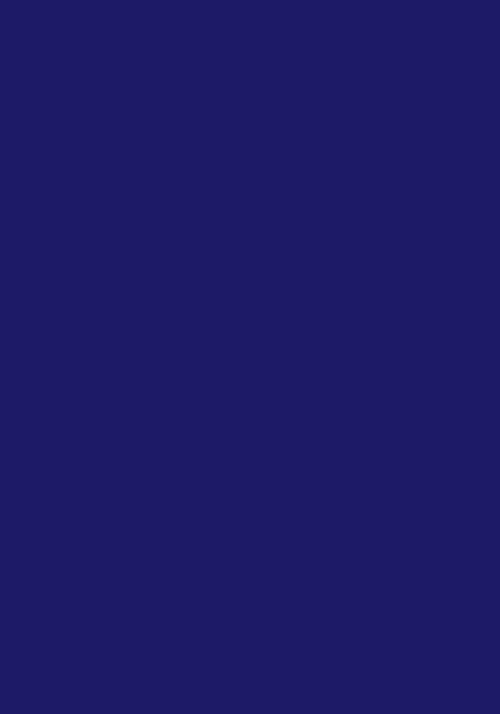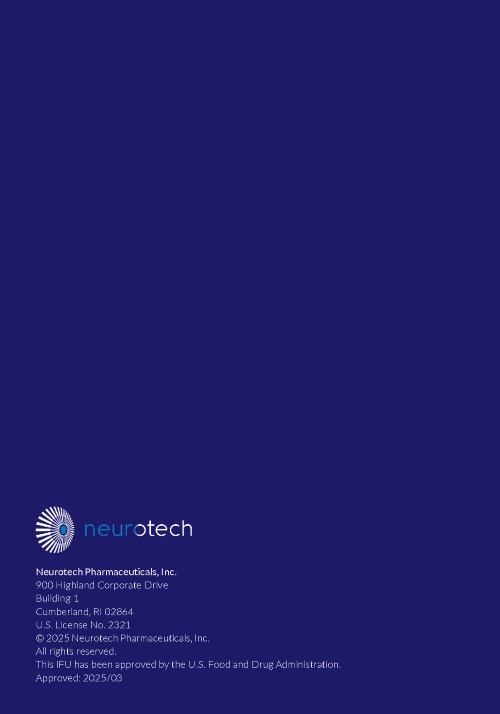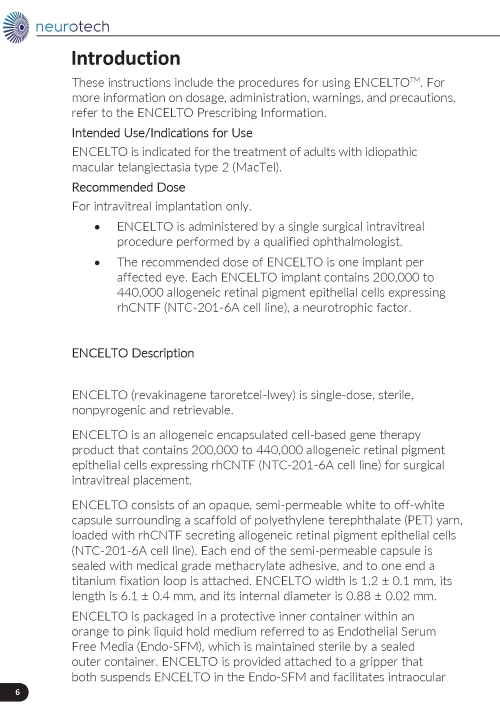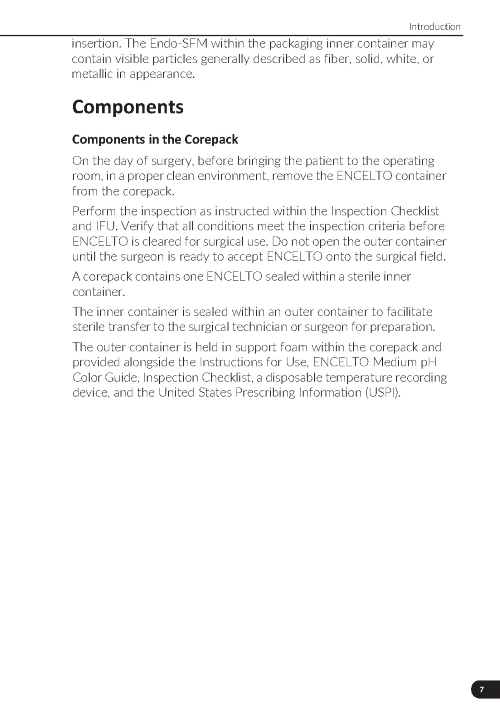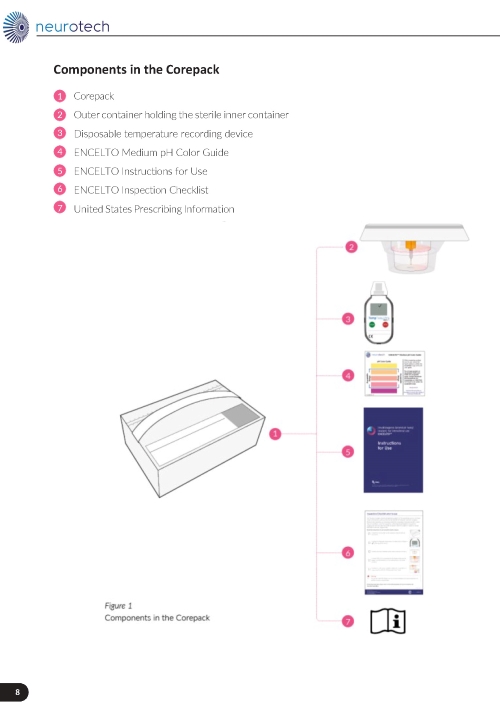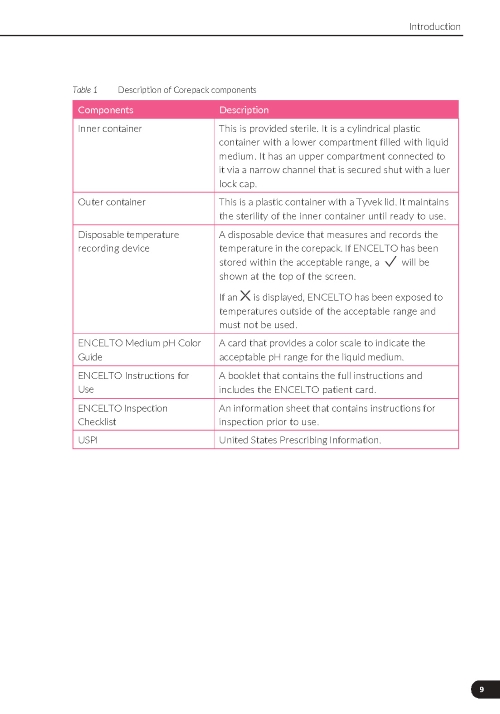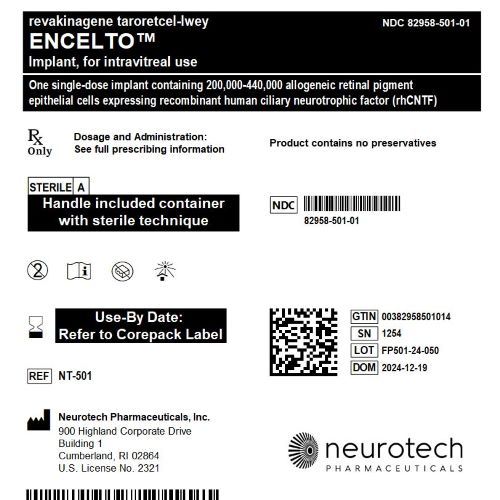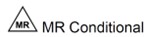 DRUG LABEL: ENCELTO
NDC: 82958-501 | Form: IMPLANT
Manufacturer: Neurotech Pharmaceuticals, Inc.
Category: prescription | Type: HUMAN PRESCRIPTION DRUG LABEL
Date: 20250321

ACTIVE INGREDIENTS: REVAKINAGENE TARORETCEL 440000 [arb'U]/1 1

HIGHLIGHTS OF PRESCRIBING INFORMATION

These highlights do not include all the information needed to use ENCELTO™ safely and effectively. See full prescribing information for ENCELTO.
ENCELTO (revakinagene taroretcel-lwey) implant, for intravitreal use
Initial U.S. Approval: 2025

1 INDICATIONS AND USAGE

ENCELTO is an allogeneic encapsulated cell-based gene therapy indicated for the treatment of adults with idiopathic macular telangiectasia type 2 (MacTel).

2 DOSAGE AND ADMINISTRATION

For intravitreal implantation only.

- ENCELTO is intended for surgical intravitreal implantation under aseptic conditions by a qualified ophthalmologist. (2.1)
- The recommended dose is one ENCELTO implant per affected eye containing 200,000 to 440,000 allogeneic retinal pigment epithelial cells expressing recombinant human ciliary neurotrophic factor (rhCNTF). (2.1)
- Carefully inspect ENCELTO prior to use and refer to the Instructions for Use when preparing for and performing surgical placement or removal of ENCELTO. (2.2, 2.3)

3 DOSAGE FORMS AND STRENGTHS

One single-dose implant containing 200,000 to 440,000 allogeneic retinal pigment epithelial cells expressing rhCNTF.

4 CONTRAINDICATIONS

- Ocular or periocular infections. (4)
- Known hypersensitivity to Endothelial Serum Free Media (Endo-SFM). (4)

5 WARNINGS AND PRECAUTIONS

- ENCELTO implantation has been associated with severe vision loss, infectious endophthalmitis, retinal tears and/or detachment, vitreous hemorrhage, implant extrusion, cataract formation, suture related complications, and delayed dark adaptation. Patients should be instructed to report signs or symptoms that could be associated with these events without delay. Additional surgical and/or medical management may be required. (5.1, 5.2, 5.3, 5.4, 5.5, 5.6, 5.7, 5.8)

- Vitreous Hemorrhage: Temporarily discontinue antithrombotic medication prior to ENCELTO insertion surgery to reduce the risk of implantation related vitreous hemorrhage. Vitreous hemorrhages occurring greater than one year from implantation could be a sign of ENCELTO extrusion. The surgical site should be examined closely and the ENCELTO should be surgically repositioned if indicated. (5.4)

6 ADVERSE REACTIONS

The most common adverse reactions (incidence ≥2%) were conjunctival hemorrhage, delayed dark adaptation, foreign body sensation, eye pain, suture related complications, miosis, conjunctival hyperemia, eye pruritus, ocular discomfort, vitreous hemorrhage, blurred vision, headache, dry eye, eye irritation, cataract progression or formation, vitreous floaters, severe vision loss, eye discharge, anterior chamber cell, iridocyclitis. (6.1)

To report SUSPECTED ADVERSE REACTIONS, contact Neurotech at 1-833-963-9275 or FDA at 1-800-FDA-1088 or www.fda.gov/medwatch.

FULL PRESCRIBING INFORMATION

1 INDICATIONS AND USAGE

ENCELTO is indicated for the treatment of adults with idiopathic macular telangiectasia type 2 (MacTel).

2 DOSAGE AND ADMINISTRATION

2.1 Recommended Dose

For intravitreal implantation only

• ENCELTO is administered by a single surgical intravitreal procedure performed by a qualified ophthalmologist.

• The recommended dose is one ENCELTO implant per affected eye. Each ENCELTO implant contains 200,000 to 440,000 allogeneic retinal pigment epithelial cells expressing recombinant human ciliary neurotrophic factor (rhCNTF) (NTC-201-6A cell line), a neurotrophic factor.

2.2 ENCELTO Surgical Placement

The ENCELTO implant insertion is a surgical procedure performed in an operating room under aseptic conditions by a qualified ophthalmologist.

Pre-Surgical Preparation

1. Inspect the ENCELTO packaging for any signs of damage or leakage.
2. Verify the use-by date.
3. Confirm that the disposable temperature recording device displays a checkmark at the top of the screen.
4. Ensure the liquid medium is at the correct pH using the provided pH color guide reference card.

Prepare the surgical field properly.

Surgical Steps

1. Preparing the Surgical Site

a. Create a 7x7 mm peritomy of the conjunctiva and Tenon’s capsule at the selected implantation site.

b. Place a corneal-limbal traction suture in the selected surgical quadrant (either inferotemporal or inferonasal) (Figure 1).

c. Maintain hemostasis of the underlying sclera and conjunctiva (Figure 1).

d. Using an MVR and 15-degree blade, create a 3.0 mm full-thickness sclerotomy 3.75 mm posterior and parallel to the limbus (Figure 2). Do not insert ENCELTO outside of the pars plana.

e. Confirm:

• The incision is full thickness.

• There is adequate hemostasis.

• There is no spanning uveal tissue.

2. Preparing the ENCELTO Implant

a. Open the inner container and expose the upper compartment and luer lock cap (Figure 3).

b. Unlock the luer lock cap by turning it counterclockwise once.

c. Lift the luer lock cap vertically to remove ENCELTO (attached to the gripper).

d. Rinse ENCELTO with at least 5 mL of sterile Balanced Saline Solution (BSS).

e. Keep ENCELTO moist by applying BSS every 10 minutes until insertion.

f. While holding the luer lock cap, pass a double-armed 9-0 polypropylene suture needle through ENCELTO’s fixation loop (Figure 4).

3. Implantation of ENCELTO

a. Gently open the sclerotomy incision and insert ENCELTO perpendicularly into the eye (Figure 5).

b. Ensure only the fixation loop is exposed.

c. Release ENCELTO from the gripper by squeezing the indicated region with forceps or a fine needle holder (Figure 6).

4. Securing the Implant

a. Secure ENCELTO by creating a 3-1-1 anchor knot with the polypropylene suture at the apex of the fixation loop (Figure 7).

b. Confirm ENCELTO is centered in the incision.

c. Pass each suture arm centrally through either side of the wound at 90-99% scleral depth (Figure 8).

d. Pull up the suture ends and confirm that the fixation loop is at the proper depth (90-99%).

e. Tie down the suture to the sclera with a 3-1-1 knot, ensuring the knot is placed away from the incision.

f. If a suture breaks, leave the tail as long as possible and lay it flat.

g. Take a 2.0 mm scleral bite at 50-75% depth beyond the sclerotomy on each side (Figure 9).

5. Closing the Incision

a. Close the scleral incision with 9-0 nylon sutures (Figure 10), ensuring:

- The polypropylene suture is captured to prevent irritation and erosion.
- All nylon suture knots are rotated into the sclera.
- The closure is watertight.

b. Pull the polypropylene suture end taut and cut it flush to the sclera.

c. Close the conjunctiva and Tenon’s capsule using 6-0 plain gut or chromic suture, or 7-0 Vicryl suture or similar.

d. Ensure Tenon’s capsule covers the insertion site and use 3-point fixation and scleral bites.

e. Administer sub-conjunctival steroid injection: dexamethasone, 2 mg/0.5 ml (4 mg/ml) or equivalent. If the case is complicated and inflammation is anticipated, a higher dose of dexamethasone (0.5 cc of 10 mg/ml) or equivalent may be used, at the surgeon’s discretion.

f. Perform indirect ophthalmoscopy to confirm placement of ENCELTO in the vitreous and that there are no intraocular complications. Failure to perform indirect ophthalmoscopy can lead to unidentified malpositioning of ENCELTO and intraocular complications.

Post-Operative Wound Care

- The patient is to use:
  - A topical antibiotic solution at a frequency of 1 drop four times a day for 7 days.
  - A steroid drop taper of prednisolone acetate 1% (or equivalent) starting the day after surgery with the following taper:
    - 1 drop four times a day for the first 7 days;
    - 1 drop three times a day for the next 7 days;
    - 1 drop two times a day for the next 7 days;
    - 1 drop once a day for the last 7 days.

Refer to ENCELTO Instructions for Use for detailed guidance on implantation procedure.

2.3 ENCELTO Removal Procedure

Removal of ENCELTO is a surgical procedure performed in an operating room under aseptic conditions by a qualified ophthalmologist. Remove ENCELTO implant, if vitrectomy with a complete gas fill or silicone oil fill is required or if infectious endophthalmitis occurs.

Surgical Steps

1. Preparing the Surgical Site (Figure 11)

a. Create a 7x7 mm peritomy of the conjunctiva and Tenon’s capsule to expose the insertion site.

b. Place a corneal-limbal traction suture in the quadrant where ENCELTO is located.

c. Maintain hemostasis of the sclera and surrounding conjunctiva.

2. Establishing Infusion & Vitrectomy (Figure 12)

a. Place an infusion cannula in the inferior quadrant (opposite ENCELTO).

b. Confirm the infusion line is positioned within the vitreous cavity before opening the infusion.

c. Insert two superior cannulas following normal pars plana vitrectomy protocol.

d. Perform a thorough vitrectomy to remove vitreous surrounding ENCELTO without disrupting the hollow fiber membrane.

3. Reopening the Sclerotomy

a. Locate the ENCELTO incision and remove the two nylon sutures while leaving the polypropylene suture intact (Figure 13).

b. Using an MVR blade, carefully dissect open the original scleral incision down to the ENCELTO cap at the base of the fixation loop (Figure 14).

c. Extend the incision along the entire 3.0 mm length to full thickness.

d. Cut the polypropylene anchor suture on the anterior side of the knot.

e. Turn off or lower infusion pressure.

4. Removing ENCELTO (Figure 15)

a. Fully open the pars plana sclerotomy and confirm there is no spanning uveal tissue.

b. Identify and grasp the fixation loop.

c. Cut off the remaining polypropylene knot.

d. Remove ENCELTO from the eye.

e. Inspect the ENCELTO capsule for any damage or penetration.

f. Do not discard or dispose of the ENCELTO implant. Call and report to 1-833-963-9275. The appropriate action will be taken to initiate the return of ENCELTO and possible replacement.

5. Closing the Incision

a. Remove any prolapsed vitreous.

b. Close the sclerotomy with interrupted 7-0 Vicryl sutures for a watertight closure.

c. Remove the infusion line and additional cannulas.

d. Close the conjunctiva with 6-0 plain gut sutures or equivalent.

Post-Operative Wound Care

- The patient is to use:
  - A topical antibiotic solution at a frequency of 1 drop four times a day for 7 days.
  - A steroid drop taper of prednisolone acetate 1% (or equivalent) starting the day after surgery with the following taper:
    - 1 drop four times a day for the first 7 days;
    - 1 drop three times a day for the next 7 days;
    - 1 drop two times a day for the next 7 days;
    - 1 drop once a day for the last 7 days.

Refer to ENCELTO Instructions for Use for detailed guidance on removal procedure.

3 DOSAGE FORMS AND STRENGTHS

ENCELTO is a single-dose implant that contains 200,000 to 440,000 allogeneic retinal pigment epithelial cells expressing recombinant human ciliary neurotrophic factor (rhCNTF) (NTC-201-6A cell line) for intravitreal surgical placement. ENCELTO is an opaque semi-permeable capsule that is white to off-white, capped on both ends, and has a titanium loop on one end. The ENCELTO width is 1.2 ± 0.1 mm, its length is 6.1 ± 0.4 mm, and its internal diameter is 0.88 ± 0.02 mm (Figure 17).

4 CONTRAINDICATIONS

ENCELTO is contraindicated in patients with:

- Active or suspected ocular or periocular infections.
- Known hypersensitivity to Endothelial Serum Free Media (Endo-SFM)

5 WARNINGS AND PRECAUTIONS

5.1 Severe Vision Loss

Severe vision loss defined as three or more lines of visual acuity loss [≥15 Early Treatment Diabetic Retinopathy Study (ETDRS) letters] has occurred following ENCELTO implantation [see Adverse Reactions (6)]. Monitor patients for signs and symptoms of vision loss and manage as clinically indicated.

5.2 Infectious Endophthalmitis

Infectious endophthalmitis may occur following ENCELTO implantation. Signs and symptoms of infectious endophthalmitis include progressively worsening eye pain, vision loss, or scleral and conjunctival injection. To mitigate the risk of endophthalmitis, use proper aseptic surgical technique for ENCELTO implantation [see Dosage and Administration (2.2)]. Monitor patients for signs or symptoms of infectious endophthalmitis. Remove ENCELTO implant if infectious endophthalmitis occurs and manage symptoms according to clinical practice.

5.3 Retinal Tear and Detachment

Retinal tears and retinal detachment may occur following ENCELTO implantation. Signs and symptoms of retinal tears include acute onset of flashing lights, floaters, and/or loss of visual acuity. Signs and symptoms of retinal detachment may include progressive visual field loss and/or loss of visual acuity. Use standard vitreoretinal surgical techniques during ENCELTO implantation to minimize the risk of retinal tears and retinal detachment. Monitor for any signs or symptoms of retinal tear and/or retinal detachment. Treat rhegmatogenous retinal detachment and retinal tears promptly. Remove ENCELTO implant, if vitrectomy with a complete gas fill or silicone oil fill is required [see Dosage and Administration (2.3)].

5.4 Vitreous Hemorrhage

Vitreous hemorrhage, which may result in temporary vision loss, has occurred following ENCELTO implantation [see Adverse Reactions (6)]. Patients receiving antithrombotic medication (e.g., oral anticoagulants, aspirin, nonsteroidal anti-inflammatory drugs) may be at increased risk of vitreous hemorrhage. To reduce the risk of vitreous hemorrhage, interrupt antithrombotic medications prior to the ENCELTO implantation. Vitrectomy surgery may be necessary to clear severe, recurrent, or non-clearing vitreous hemorrhage. If the patient has a late onset vitreous hemorrhage (greater than one year following ENCELTO implantation surgery), examine the ENCELTO implantation site for possible implant extrusion. If implant extrusion has occurred, surgically reposition ENCELTO [see Implant Extrusion (5.5)].

5.5 Implant Extrusion

Implant extrusion through the initial scleral wound has occurred following ENCELTO implantation [see Adverse Reactions (6)]. Signs and symptoms of implant extrusion include recurrent uveitis, vitreous hemorrhage, eye pain more than one year after implantation, or visibility of titanium fixation loop under the conjunctiva. To reduce the risk of implant extrusion, carefully follow the specific surgical steps for ENCELTO implantation [see Dosage and Administration (2.2)].

Evaluate patients after 6 months to confirm proper positioning of ENCELTO and then annually. If ENCELTO begins to extrude, surgically reposition ENCELTO to a proper scleral wound depth either in the same site or in the opposing inferior quadrant of the vitreous cavity.

5.6 Cataract Formation

Cataract formation, including cataract cortical, cataract nuclear, cataract subcapsular, cataract traumatic, and lenticular opacities, has occurred following ENCELTO implantation [see Adverse Reactions (6)]. To reduce the risk of ENCELTO-related cataract formation or progression, carefully follow the specific surgical steps for ENCELTO implantation [see Dosage and Administration (2.2)].

5.7 Suture Related Complications

Suture related complications, including conjunctival erosions due to suture tips and suture knots, have occurred following ENCELTO implantation [see Adverse Reactions (6)]. To mitigate the risk of suture related complications, carefully follow the specific surgical steps for ENCELTO implantation [see Dosage and Administration (2.2)] and manage suture-related complications as clinically indicated.

5.8 Delayed Dark Adaptation

Delayed Dark Adaptation, a delay in the ability to adjust vision from a bright lighting condition to a dim lighting, has occurred following ENCELTO administration which remained unchanged for the duration of study follow up [see Adverse Reactions (6)]. Advise patients to take caution while driving and navigating in the dark.

6 ADVERSE REACTIONS

6.1 Clinical Trials Experience

Because clinical trials are conducted under widely varying conditions, adverse reaction rates observed in the clinical trials of a drug cannot be directly compared to rates in the clinical trials of another drug and may not reflect the rates observed in practice.

The safety data described in this section reflects exposure to ENCELTO in two clinical trials, Study 1 (NTMT-03-A) and Study 2 (NTMT-03-B) and are pooled for analysis. A total of 117 patients received ENCELTO, and 111 patients underwent a sham procedure and were followed for a duration of 24 months [see Clinical Studies (14)].

Serious adverse reactions occurred in six patients (5%) including suture related complications (n=5) and implant extrusion (n=1).

Table 1 lists the most common adverse reactions that occurred in >2% patients and with higher frequency in ENCELTO group compared to Sham group in Study 1 and Study 2.

Table 1. Adverse Reactions occurring in ≥2% of Patients and with higher frequency in ENCELTO group compared to Sham group in ENCELTO studies*
Adverse Reactions | ENCELTO; (N=117); n (%) | Sham; (N=111); n (%)
Conjunctival hemorrhage | 36 (31) | 29 (26)
Delayed dark adaptation | 27 (23.1) | 1 (1)
Foreign body sensation in eyes | 18 (15) | 15 (13.5)
Eye pain | 18 (15) | 10 (9)
Suture related complication** | 18 (15.4) | 3 (2.7)
Miosis | 18 (15.4) | 0 (0.0)
Conjunctival hyperemia | 13 (11) | 9 (8)
Eye pruritus | 10 (9) | 4 (3.6)
Ocular discomfort | 10 (9) | 1 (1)
Vitreous hemorrhage | 10 (8.5) | 0 (0.0)
Vision blurred | 8 (7) | 4 (4)
Headache | 8 (7) | 1 (1)
Dry eye | 7 (6) | 2 (2)
Eye irritation | 6 (5.1) | 2 (2)
Cumulative cataract incidence | 6 (5) | 0 (0)
Vitreous floaters | 6 (5) | 0 (0.0)
Severe visual loss>15 letters*** | 4 (3) | 0 (0)
Eye discharge | 4 (3.4) | 1 (0.9)
Anterior chamber cell | 4 (3.4) | 0 (0.0)
Iridocyclitis | 3 (2.6) | 0 (0)

* Pooled data from Study 1 and Study 2; Adverse reaction rates were comparable between the two studies
**Suture related complications include exposed suture, foreign body sensation, conjunctival wound dehiscence, painful sutures, suture irritation, suture granuloma, scleral wound opening, and itchy suture
*** Includes one case of visual loss due to cataract formation which remained unresolved at the end of the study

8 USE IN SPECIFIC POPULATIONS

8.1 Pregnancy

Risk Summary

There are no data on the use of ENCELTO in pregnant women. Endogenous CNTF is naturally found in maternal plasma, placental cells, and umbilical cord blood. It is not known if the use of ENCELTO increases CNTF above naturally occurring levels in these tissues.

In animal reproduction studies, subcutaneous administration of rhCNTF to pregnant rats and rabbits demonstrated no evidence of teratogenic effects on the fetus. However, when administered to rabbits at a dose level of 10ug/kg/day, a decrease in implantations and live fetuses was observed. When administered to rats at a dose level of 100ug/kg/day a decrease in corpora lutea was observed.

The estimated background risk of major birth defects and miscarriage in the indicated population is unknown. All pregnancies have a background risk of birth defect, loss, or other adverse outcomes. In the U.S. general population, the estimated background risk of major birth defects is 2% to 4% and of miscarriage is 15% to 20% of clinically recognized pregnancies.

Data

Animal Data

See Risk Summary for details on data.

8.2 Lactation

Risk Summary

There is no data on the presence of ENCELTO in human milk, its effects on the breastfed infant, or its impact on milk production.

The developmental and health benefits of breastfeeding should be considered along with the mother's clinical need for ENCELTO and any potential adverse effects on the breastfed infant from rhCNTF or from the underlying maternal condition.

8.4 Pediatric Use

The safety and effectiveness of ENCELTO have not been established in pediatric patients.

8.5 Geriatric Use

There were 38 patients (32%) 65 years of age and older and two patients (1%) 75 years of age and older in Study 1 and Study 2 who received ENCELTO [see Clinical Studies (14)]. Clinical studies of ENCELTO did not include sufficient numbers of patients aged 65 and over to determine whether they respond differently than younger patients.

11 DESCRIPTION

ENCELTO (revakinagene taroretcel-lwey) implant, is single-dose, sterile, nonpyrogenic and retrievable.

ENCELTO is an allogeneic encapsulated cell-based gene therapy that contains 200,000 to 440,000 allogeneic retinal pigment epithelial cells expressing recombinant human ciliary neurotrophic factor (rhCNTF) (NTC-201-6A cell line) for surgical intravitreal placement.

ENCELTO consists of an opaque, semi-permeable white to off-white capsule surrounding a scaffold of polyethylene terephthalate (PET) yarn, loaded with rhCNTF secreting allogeneic retinal pigment epithelial cells (NTC-201-6A cell line). Each end of the semi-permeable capsule is sealed with medical grade methacrylate adhesive, and to one end a titanium fixation loop is attached. ENCELTO width is 1.2 ± 0.1 mm, length is 6.1 ± 0.4 mm, and its internal diameter is 0.88 ± 0.02 mm (Figure 17).

ENCELTO is packaged in a protective inner container within an orange to pink liquid hold medium referred to as Endothelial Serum Free Media (Endo-SFM), which is maintained sterile by a sealed outer container. ENCELTO is provided attached, by the fixation loop, to a gripper that both suspends ENCELTO in the Endo-SFM and facilitates intraocular insertion. The Endo-SFM within the packaging inner container may contain visible particles generally described as fiber, solid, white, or metallic in appearance.

ENCELTO is manufactured using animal and human derived reagents.

12 CLINICAL PHARMACOLOGY

12.1 Mechanism of Action

ENCELTO secretes recombinant human ciliary neurotrophic factor (rhCNTF), which is one of several neurotrophic factors endogenously produced by neurons and supporting glial cells. Exogenous CNTF is thought to initially target Müller glia to trigger a cascade of signaling events that may promote photoreceptor survival; however, the mechanism of action for ENCELTO is not completely understood.

12.3 Pharmacokinetics

Systemic exposure of rhCNTF was measured in 2 distribution studies in rabbits and in 2 toxicology studies in minipigs. Overall, there was no evidence of systemic exposure to rhCNTF after implantation of ENCELTO in rabbits for periods up to 9 months or in minipigs for periods of up to 6 months.

Following intraocular implantation of a single ENCELTO dose in rabbits at 12 weeks, the mean Cmax of rhCNTF in the vitreous and aqueous was 2.0 and 0.3 ng/mL, respectively, and below the level of quantitation (LLOQ) in the serum and contralateral, untreated eye. Similarly in human patients, rhCNTF levels were below the limit for LLOQ in the serum.

12.6 Immunogenicity

The observed incidence of anti-drug antibodies is highly dependent on the sensitivity and specificity of the assay. Differences in assay methods preclude meaningful comparisons of the incidence of anti-drug antibodies in the studies described below with the incidence of anti-drug antibodies in other studies, including those of ENCELTO or of other products.

In a six-month Study NTMT-02B in which patients received ENCELTO in a single eye, one out of 31 patients (3%) tested positive for serum antibodies against the ENCELTO secreted product protein rhCNTF and one patient (3%) tested positive to serum non-secreted intracellular protein DHFR.

Because of the low occurrence of anti-drug antibodies, the effect of serum anti-rhCNTF and anti-DHFR antibodies on the safety or efficacy of ENCELTO is unknown.

13 NONCLINICAL TOXICOLOGY

13.1 Carcinogenesis, Mutagenesis, Impairment of Fertility

Carcinogenesis and Mutagenesis

No carcinogenicity or mutagenicity studies have been conducted with rhCNTF.

Impairment of Fertility

In male rats, fertility was unaffected at subcutaneous doses of rhCNTF up to 300 μg/kg/day.

See Pregnancy (8.1) for data regarding effects on female fertility.

14 CLINICAL STUDIES

The efficacy of ENCELTO was evaluated in two studies, Study NTMT-03-A (NCT03316300; Study 1) and Study NTMT-03-B (NCT03319849; Study 2) as described below.

Study 1

Study 1 was a randomized, multi-center, sham-controlled study which enrolled adults with MacTel. For enrollment, the patients were required to have a photoreceptor inner segment/outer segment (IS/OS PR) break (loss) in ellipsoid zone (EZ) between 0.16 and 2.00 mm^2 measured by spectral domain-optical coherence tomography (SD-OCT) and best corrected visual acuity (BCVA) of 54-letter score or better (20/80 or better) as measured by the Early Treatment Diabetic Retinopathy Study (ETDRS) chart at screening. Patients with neovascular MacTel were excluded. Patients were randomized to receive either ENCELTO intravitreal implant or sham procedure under standard operative procedures. Patients in ENCELTO group underwent conjunctival peritomy, implant placement in the vitreous cavity via sclerotomy and closure with sutures. Patients in the Sham group underwent conjunctival peritomy, scleral pressure, and conjunctival closure with sutures. One hundred and fifteen (96%) of 120 patients underwent the assigned procedure and were included in the analysis of efficacy.

A total of 120 patients were randomized and of these, 115 patients (ENCELTO group: 58; Sham group: 57) comprise the efficacy analysis population. The demographic characteristics of the efficacy analysis population were as follows: the mean age was 61 years (range 40 to 78 years), 79 patients (69%) were female, 98 patients (85%) were White, 5 patients (4%) were Asian, 3 patients (3%) were Black or African American, 1 patient (1%) was American Indian, and 8 patients (7%) were of “other” race. Six patients (5%) were Hispanic. The median (min, max) baseline EZ area loss was 0.35 (0.15, 1.99) mm^2 for the ENCELTO group and 0.36 (0.16, 1.7) mm^2 for the Sham group. The median (min, max) baseline aggregate sensitivity of microperimetry within the EZ break area 35.2 (0.75, 398.8) dB for the ENCELTO group and 35.5 (2, 281.3) dB for the Sham group.

The primary efficacy outcome measure was the rate of change in the area of EZ loss (IS/OS, macular PR loss) over 24 months, as measured by SD-OCT. The secondary outcome measure was the mean change in aggregate sensitivity loss of microperimetry within the EZ break area from baseline to Month 24.

The efficacy outcome results for Study 1 are summarized in Table 2.

Table 2. Efficacy Results for Study 1 (N=115)
Efficacy endpoints | ENCELTO; n= 58 | Sham; n=57 | Difference; ENCELTO-Sham | P-valuec
Rate of change in EZ area loss from baseline over 24 monthsa; mm^2; (95% CI) | 0.075; (0.05, 0.10) | 0.166; (0.14, 0.19) | -0.091; (-0.13, -0.06) | <0.0001
Mean change in aggregate retinal sensitivity loss from baseline to 24-monthsb; dB; (95% CI) | 25.27; (15.88, 34.67) | 43.02; (31.78, 54.26) | -17.75; (-32.58, -2.91) | 0.02

CI = confidence interval, EZ=ellipsoid zone

a Estimated by using a longitudinal mixed model including EZ area loss as the dependent variable, patient-specific random intercepts, treatment group, time (continuous), and interaction between treatment and time as covariates. The baseline and Months 12, 16, 20, and 24 visits were included.

b Estimated by using two-sample t-test; seven ENCELTO and four Sham patients were excluded due to missing data.

c Statistically significant at two-sided alpha of 0.05.

Study 2

Study 2 was a randomized, multi-center, sham-controlled study which enrolled adult with MacTel. For enrollment, the patients were required to have an IS/OS PR break in EZ between 0.16 and 2.00 mm^2 measured by SD-OCT and BCVA of 54-letter score or better (20/80 or better) as measured by the ETDRS chart at screening. Patients with neovascular MacTel were excluded.

Patients were randomized to receive either ENCELTO intravitreal implant or sham procedure under standard peri-operative procedures. Patients in ENCELTO group underwent conjunctival peritomy, implant placement in the vitreous cavity via sclerotomy and closure with sutures. Patients in the Sham group underwent conjunctival peritomy, scleral pressure, and conjunctival closure with sutures. One hundred and thirteen (95%) of the 119 patients underwent the assigned procedure and were included in efficacy evaluation.

A total of 119 patients were randomized and of these, 113 patients (ENCELTO group: 59; Sham group: 54) comprise the efficacy analysis population. The demographic characteristics of the efficacy analysis population were as follows: the mean age was 59 years (range: 40 to 75 years), 82 patients (73%) were female, 102 patients (90%) were White, 4 patients (4%) were Asian, and 7 patients (6%) were of “other” race or “unable to specify” race. Eight patients (7%) were Hispanic. The median (min, max) baseline EZ area loss was 0.48 (0.16, 1.63) mm^2 for the ENCELTO and 0.39 (0.16, 1.38) mm^2 for the Sham group. The median (min, max) baseline aggregate sensitivity of microperimetry within the EZ break area 40.07 (4.82, 291.52) dB for the ENCELTO group and 28.86 (0.33, 221.17) dB for the Sham group.

The primary efficacy outcome measure was the rate of change in the area of EZ loss (IS/OS, macular PR loss) over 24 months, as measured by SD-OCT. The secondary outcome measure was the mean change in aggregate sensitivity loss of microperimetry within the EZ break area from baseline to Month 24.

The efficacy results from Study 2 are summarized in Table 3 below.

Table 3. Efficacy Results for Study 2 (N=113)
Efficacy endpoints | ENCELTO; n= 59 | Sham; n=54 | Difference; ENCELTO-Sham | P-valuec
Rate of change in EZ area loss from baseline over 24 monthsa; mm^2; (95% CI) | 0.111; (0.08, 0.14) | 0.160; (0.13, 0.19) | -0.049; (-0.089, -0.008) | 0.0186c
Mean change in aggregate retinal sensitivity loss from baseline to 24-monthb; dB; (95% CI) | 40.02; (26.08, 53.96) | 41.97; (30.34, 53.60) | -1.95; (-20.33, 16.43) | 0.83

CI = confidence interval, EZ=ellipsoid zone

a Estimated by using a longitudinal mixed model including EZ area loss as the dependent variable, patient-specific random intercepts, treatment group, time (continuous), and interaction between treatment and time as covariates. The baseline and Months 12, 16, 20, and 24 visits were included.

b Estimated by using two-sample t-test; Seven ENCELTO and six Sham patients were excluded due to missing data.

c Statistically significant at two-sided alpha of 0.05.

16 HOW SUPPLIED/STORAGE AND HANDLING

16.1 How Supplied

ENCELTO is supplied as a sterile, single-dose, implant that contains 200,000 to 440,000 allogeneic retinal pigment epithelial cells expressing rhCNTF (NTC-201-6A cell line).

ENCELTO is packaged in a protective inner container within an Endothelial Serum Free Media (Endo-SFM), which is maintained sterile by a sealed outer container. ENCELTO is provided attached to a gripper that both suspends ENCELTO in the Endo-SFM and facilitates intraocular insertion. ENCELTO contains no preservatives.

NDC: 82958-501-01

See Table 4, (Figure 16) and ENCELTO “Instructions for Use” for additional details.

Table 4. ENCELTO Corepack Contents
Components | Description
Inner container | This is provided sterile. It is a cylindrical plastic container with a lower compartment filled with liquid medium. It has an upper compartment connected to it via a narrow channel that is secured shut with a luer lock cap.
Outer container | This is a plastic container with a foil lid hermetically sealed. It maintains the sterility of the inner container until ready to use.
Disposable temperature recording device | A disposable device that measures and records the temperature in the package. If ENCELTO has been stored within the acceptable range, a “✓” will be shown at the top of the screen. If an “X” is displayed, ENCELTO has been exposed to temperatures outside of the acceptable range and must not be used.
ENCELTO Medium pH Color Guide | A card that provides a color scale to indicate the acceptable pH range for the liquid medium.
ENCELTO Instructions for Use | A booklet that contains the full instructions and includes the ENCELTO patient card.
ENCELTO Inspection Checklist | An information sheet that contains instructions for inspection prior to use.
USPI | United States Prescribing Information.

Figure 16. ENCELTO Corepack Contents

Figure 17. ENCELTO

Figure 18. ENCELTO Inner Container

Figure 19. pH Color Guide

16.2 Storage and Handling

1. Using the handle, remove the corepack from the larger shipping box (Figure 16).

2. Store ENCELTO in the corepack at 16º to 37ºC (61º to 99ºF) until ready for use.

3. Do not freeze or refrigerate.

4. Inspect the disposable temperature recording device. If a check mark is displayed, the ENCELTO has remained within the acceptable temperature range and may be used. If a “X” is displayed, the ENCELTO was exposed to temperatures outside the acceptable range and must not be used. Contact Neurotech immediately at (833)-963-9275.

• Protect ENCELTO from light.

5. Handle inner container (Figure 18) using sterile technique.

6. Do not use beyond the “use by” date identified on the corepack label.

7. Do not use ENCELTO if the pH is not within the acceptable range (Figure 19). Contact Neurotech immediately at (833)-963-9275.

• Prior to disposal of an ENCELTO implant per local institutional protocols, call 1-833-963-9275 for assessment of ENCELTO return or replacement.

Orange to pink liquid hold medium referred to as Endothelial Serum Free Media (Endo-SFM) within packaging inner container may contain visible particles. Particle general description fiber, solid, white, or metallic in appearance.

17 PATIENT COUNSELING INFORMATION

Advise the patient to read the FDA-approved patient labeling (Patient Information).

Discuss the following with the patient.

Advise patients that ENCELTO implantation may be associated with infectious endophthalmitis (eye infection), retinal tear and detachment (retina separates from the eye wall resulting in vision loss), vitreous hemorrhage (bleeding within the central cavity of the eye), implant extrusion, suture-related complications, cataract formation (clouding of the lens of the eye), severe vision loss, and delayed dark adaptation (ability of the eye to adjust from bright lighting conditions to dark lighting conditions) [see Warnings and Precautions (5)].

Instruct patients to seek immediate care from an ophthalmologist if they experience any signs or symptoms that could be associated with these events which may include the following:

- An increase in floaters, the appearance of “spider webs”, flashing lights, sensitivity to light, or loss of vision or visual field;
- Increasing eye pain, progressive redness in the white of the eye, a sudden sensation that something is in their eye (i.e., foreign body sensation) or eye discharge.

Advise patients that they may temporarily experience the following after ENCELTO implantation:

- Mild sensation of something in the eye (i.e., foreign body sensation)
- Eye redness, irritation, pain or discomfort, or dryness
- Blurred vision or floaters

Advise patients that delayed dark adaptation may be experienced for the length of time that ENCELTO is surgically placed [see Warnings and Precautions (5.8)]. Advise patients on the following safety precautions.

- Driving: delayed dark adaptation may impair one's ability to see objects, pedestrians, or road signs when moving rapidly from a brightly lit environment to a dimly lit environment (for example, entering a tunnel during the daytime).
- Navigating in the dark: Advise caution when moving from bright to dark areas, such as entering a dark room or stepping outside at dusk. Consider using flashlights, nightlights, or motion-activated lighting at home.
- Consider wearing sunglasses or tinted lenses in bright environments to reduce the impact of transitioning from light to dark.

Magnetic Resonance (MR) Conditional Information

ENCELTO is MR conditional. Advise patients that they have ENCELTO implanted in their eye and provide the patient with their implant card should they require Magnetic Resonance Imaging (MRI).

Driving and Using Machines

- Advise patients to not drive or use machinery until the eye shield has been removed and their ophthalmologist informs them that their vision has recovered to an acceptable level.

Postoperative Care

Advise patients on the following post operative care:

- Avoid heavy lifting (over 20 pounds) for one week.
- Keep water out of the eye (e.g., close eye while showering) for one week.
- Protect eyes by wearing glasses or protective eyewear during the day and using an eye shield at night for one week.
- Use a topical antibiotic solution at a frequency of 1 drop four times a day for 7 days.
- Use a steroid drop taper of prednisolone acetate 1% (or equivalent) starting the day after surgery with the following taper:
  - 1 drop four times a day for the first 7 days;
  - 1 drop three times a day for the next 7 days;
  - 1 drop two times a day for the next 7 days;
  - 1 drop once a day for the last 7 days.

Manufactured by:

Neurotech Pharmaceuticals, Inc.

Building 1, Suite 101

Cumberland, RI 02864

U.S. license number: 2321

PATIENT INFORMATION

ENCELTO (En-SEL-toh)

A surgical implant for use in the eye

What is ENCELTO?

ENCELTO is an encapsulated cell-based gene therapy. It is a small capsule, about the size of a grain of rice, that is placed inside the eye to release a protein called recombinant human ciliary neurotrophic factor (rhCNTF) that can directly reach the retina, the light sensitive part of the eye. The capsule contains living cells that have been genetically modified to continuously produce and release CNTF. This protein helps protect certain cells in your retina, supporting their health and reducing the loss of light-sensing cells known as photoreceptors.

ENCELTO is used to treat adults with idiopathic macular telangiectasia type 2 (MacTel); a retinal disease that causes progressive vision loss. Your ophthalmologist will assess your vision and review your medical history to determine if ENCELTO is the right treatment for you.

Who should not receive an ENCELTO surgical implant?

ENCELTO has not been tested in pediatric patients or pregnant women.

The outpatient surgical procedure should not be performed if you are currently experiencing an active or suspected eye infection.

You should not receive ENCELTO if you have a known hypersensitivity to Endothelial Serum Free Media (Endo-SFM)

Before receiving ENCELTO, tell your ophthalmologist about all your medical conditions, including:

- Are pregnant or plan to become pregnant. Although studies have shown that rhCNTF does not enter the bloodstream, its effects on an unborn baby have not been fully studied.
- Are breastfeeding or plan to breastfeed. It is not known if rhCNTF passes into your breast milk.
- Any current infections
- Are currently taking or have recently taken medicines that lower the chance of blood clots forming in the body such as warfarin, low or regular doses of aspirin, or nonsteroidal anti-inflammatory drugs (NSAID)

How is ENCELTO administered?

ENCELTO is inserted into the eye as an outpatient surgical procedure performed by an ophthalmologist experienced in retinal surgery. If removal of ENCELTO is necessary, the removal surgery must also be done by an ophthalmologist experienced in vitreoretinal surgery in an operating room as an outpatient surgery.

What should I avoid after placement of ENCELTO?

Immediately post-operative:

- Avoid heavy lifting (over 20 pounds) for one week.
- Keep water out of the eye (e.g., close your eye while showering) for one week.
- Protect your eyes by wearing glasses or protective eyewear during the day and using an eye shield at night for one week.
- Do not drive or use machinery until the eye shield has been removed and your ophthalmologist informs you that your vision has recovered to an acceptable level.

Post operative care:

- Use a topical antibiotic solution at a frequency of 1 drop four times a day for 7 days.
- Use a steroid drop taper of prednisolone acetate 1% (or equivalent) starting the day after surgery with the following taper:
  - 1 drop four times a day for the first 7 days;
  - 1 drop three times a day for the next 7 days;
  - 1 drop two times a day for the next 7 days;
  - 1 drop once a day for the last 7 days.

Magnetic Resonance (MR) Conditional Information

IMPORTANT: ENCELTO is MR conditional. You will receive an implant card, which should be shown to your imaging technician if you need Magnetic Resonance Imaging (MRI) at any time while the ENCELTO implant is in your eye. The card will include details about the ENCELTO implant, the date of insertion, and on the back, instructions for the imaging technician to access important MRI safety information.

Call your ophthalmologist for medical advice about side effects. You may report side effects to the Food and Drug Administration (FDA) at 1-800-FDA-1088.

What are the possible side effects of ENCELTO?

Please follow all post-operative instructions given by your ophthalmologist and ensure you attend all follow-up visits as recommended.

Potential side effects

Please be advised that ENCELTO and the surgical insertion has related risks such as, but not limited to, endophthalmitis (eye infection), retinal tear and detachment (retina tears and potentially separates from the eye wall resulting in vision loss), vitreous hemorrhage (bleeding within the central cavity of the eye), implant extrusion (the ENCELTO begins to work it’s way out of the eye), suture related issues (such as suture related eye irritation or exposure of sutures), temporary or permanent loss of vision, accelerated cataract formation (clouding of the lens of the eye), and delayed dark adaptation (the ability of the eye to adjust from bright lighting conditions to dark lighting conditions).

If delayed dark adaptation occurs, it is unknown for how long these symptoms will be experienced. Take the following safety precautions.

- Driving: delayed dark adaptation may impair one's ability to see objects, pedestrians, or road signs when moving rapidly from a brightly lit environment to a dimly lit environment (for example, entering a tunnel during the daytime).
- Navigating in the Dark: Take caution when moving from bright to dark areas, such as entering a dark room or stepping outside at dusk. Consider using flashlights, nightlights, or motion-activated lighting at home.
- Consider wearing sunglasses or tinted lenses in bright environments to reduce the impact of transitioning from light to dark

It is common to experience the following symptoms following ENCELTO surgery:

- Sensation of something in the eye (i.e., foreign body sensation)
- Eye redness
- Eye irritation
- Eye dryness
- Eye discharge
- Mild to moderate eye pain or discomfort
- Floaters (small spots or shapes that appear in your vision)
- Headache

When to Seek Ophthalmologist Advice

You are to seek immediate care from an ophthalmologist if there are sudden changes in your vision, such as an increase in floaters, the appearance of “spider webs,” flashing lights, sensitivity to light, loss of vision or visual field, progressively worsening eye pain, or increasing discharge/drainage from the eye as these symptoms could be a sign of a more serious issue.

General information about the safe and effective use of ENCELTO

Medicines are sometimes prescribed for purposes other than those listed in a Patient Information leaflet.

You can ask your ophthalmologist for a copy of the information about ENCELTO that is written for healthcare professionals.

You should inform your ophthalmologist that you have an ENCELTO implant inserted prior to any eye examination.

What are the ingredients in ENCELTO?

Active ingredients: ENCELTO is an encapsulated cell-based therapy that contains 200,000 to 440,000 allogeneic retinal pigment epithelial cells expressing rhCNTF (NTC-201-6A cell line), a neurotrophic factor.

Inactive ingredients: ENCELTO contains excipients (Human Endothelial Serum Free Medium (SFM) that may cause sensitivity in some patients.

Manufactured for: Treatment of idiopathic macular telangiectasia type 2 (MacTel)

Manufactured by:

Neurotech Pharmaceuticals, Inc.

Building 1, Suite 101

Cumberland, Rhode Island, 02864

This Patient Information has been approved by the U.S. Food and Drug Administration. F11002F Rev. 01
Revised: 2025/03